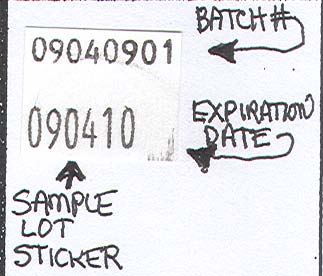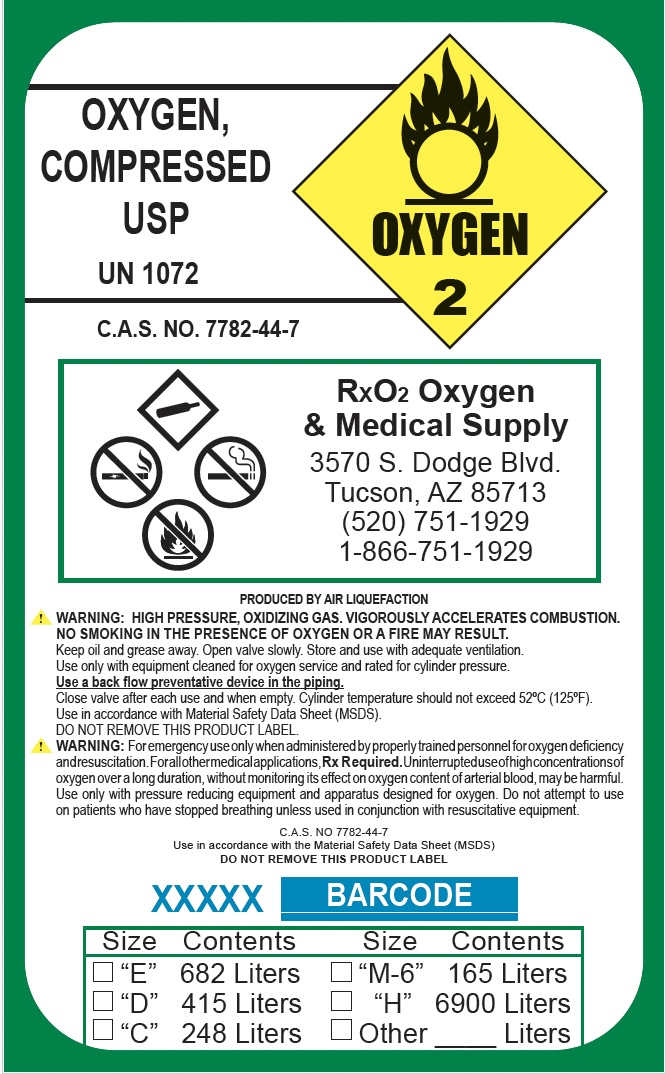 DRUG LABEL: Oxygen
NDC: 68639-0001 | Form: GAS
Manufacturer: RXO2 Oxygen & Medical Equipment Supply Co. Inc.
Category: prescription | Type: HUMAN PRESCRIPTION DRUG LABEL
Date: 20251027

ACTIVE INGREDIENTS: OXYGEN 99 L/100 L

Oxygen

Principal for Oxygen Product

OXYGEN,

COMPRESSED

USP

UN 1072
OXYGEN 2
C.A.S. NO. 7782-44-7

RXO2 Oxygen

& Medical Supply

3570 S. Dodge Blvd.

Tucson, AZ 85713

(520) 751-1929

1-866-751-1929
PRODUCED BY AIR LIQUEFACTION
WARNING: HIGH PRESSURE, OXIDIZING GAS. VIGOROUSLY ACCELERATES COMBUSTION.

NO SMOKING IN THE PRESENCE OF OXYGEN OR A FIRE MAY RESULT.

Keep oil and grease away. Open valve slowly. Store and use with adequate ventilation.

Use only with equipment cleaned for oxygen service and rated for cylinder pressure.

Use a back flow preventative device in the piping.

Close valve after each use and when empty. Cylinder temperature should not exceed 52ºC (125ºF).

Use in accordance with Material Safety Data Sheet (MSDS).
DO NOT REMOVE THIS PRODUCT LABEL.
WARNING: For emergency use only when administered by properly trained personnel for oxygen deficiency and resuscitation. For all other medical applications, Rx R equired. Uninterrupted use of high concentrations of oxygen over a long duration, without monitoring its effect on oxygen content of arterial blood, may be harmful.

Use only with pressure reducing equipment and apparatus designed for oxygen. Do not attempt to use on patients who have stopped breathing unless used in conjunction with resuscitative equipment.
C.A.S. NO 7782-44-7

Use in accordance with the Material Safety Data Sheet (MSDS)

DO NOT REMOVE THIS PRODUCT LABEL
Size Contents

“E” 682 Liters

“D” 415 Liters

“C” 248 Liters

“M-6” 165 Liters

“H” 6900 Liters

Other ____ Liters